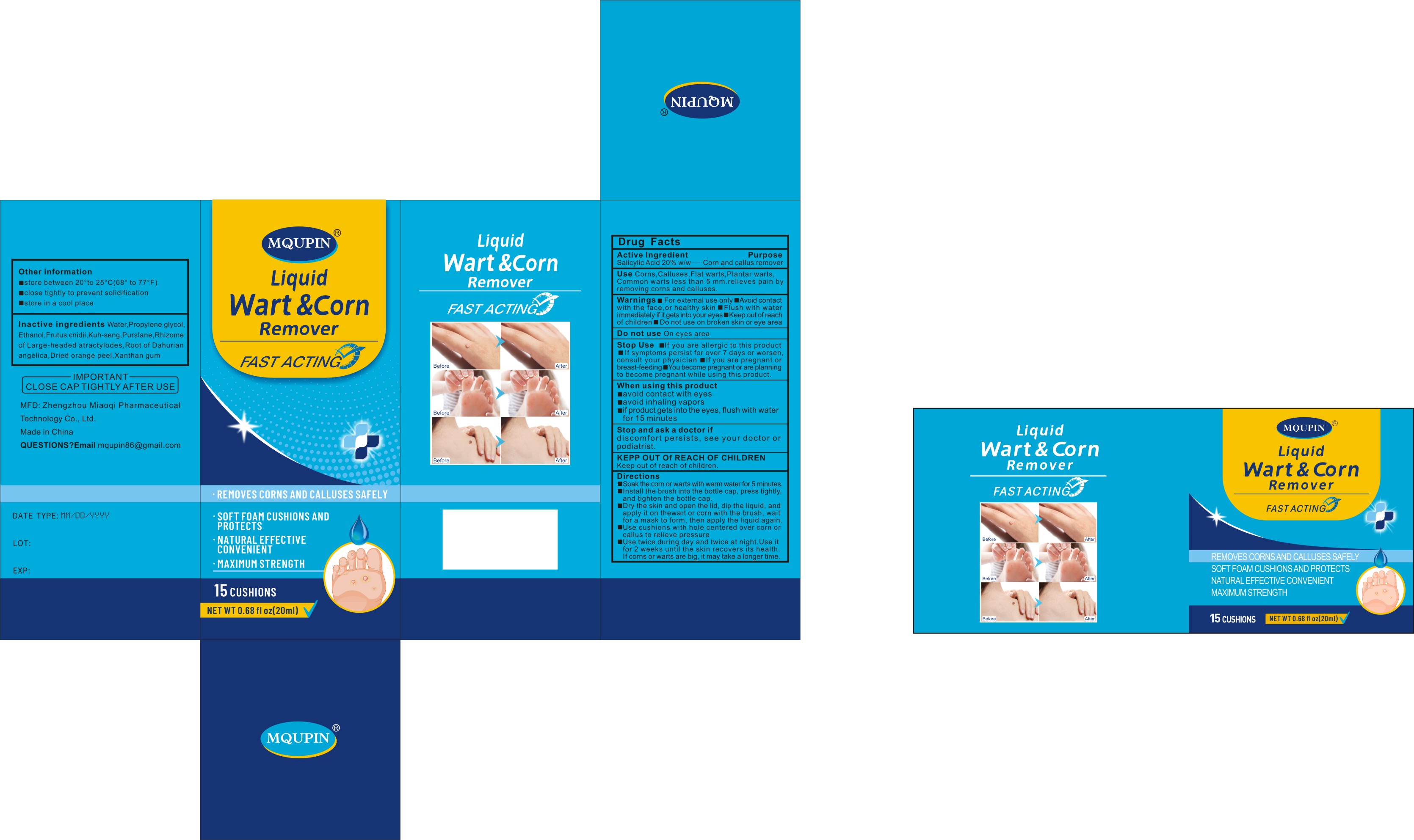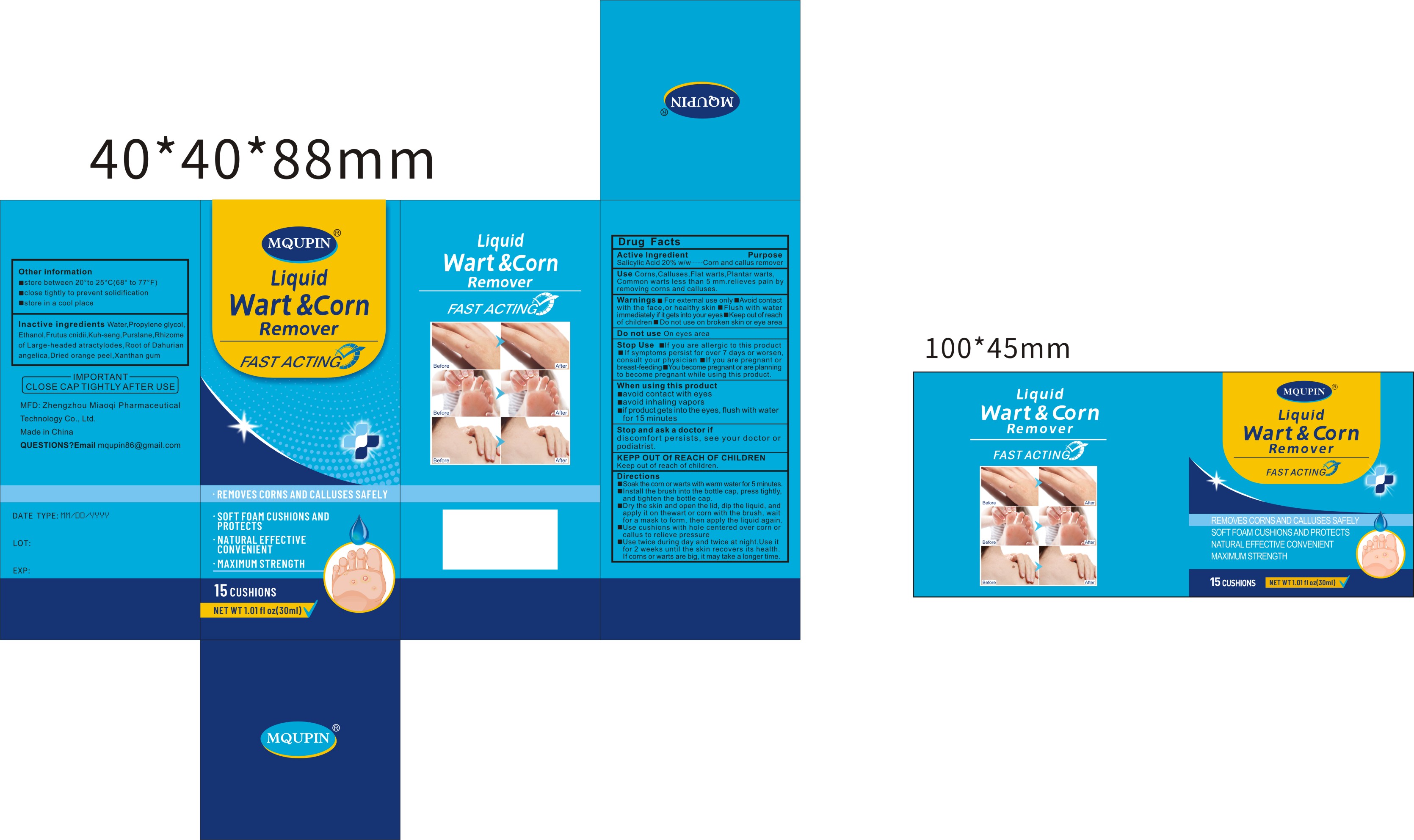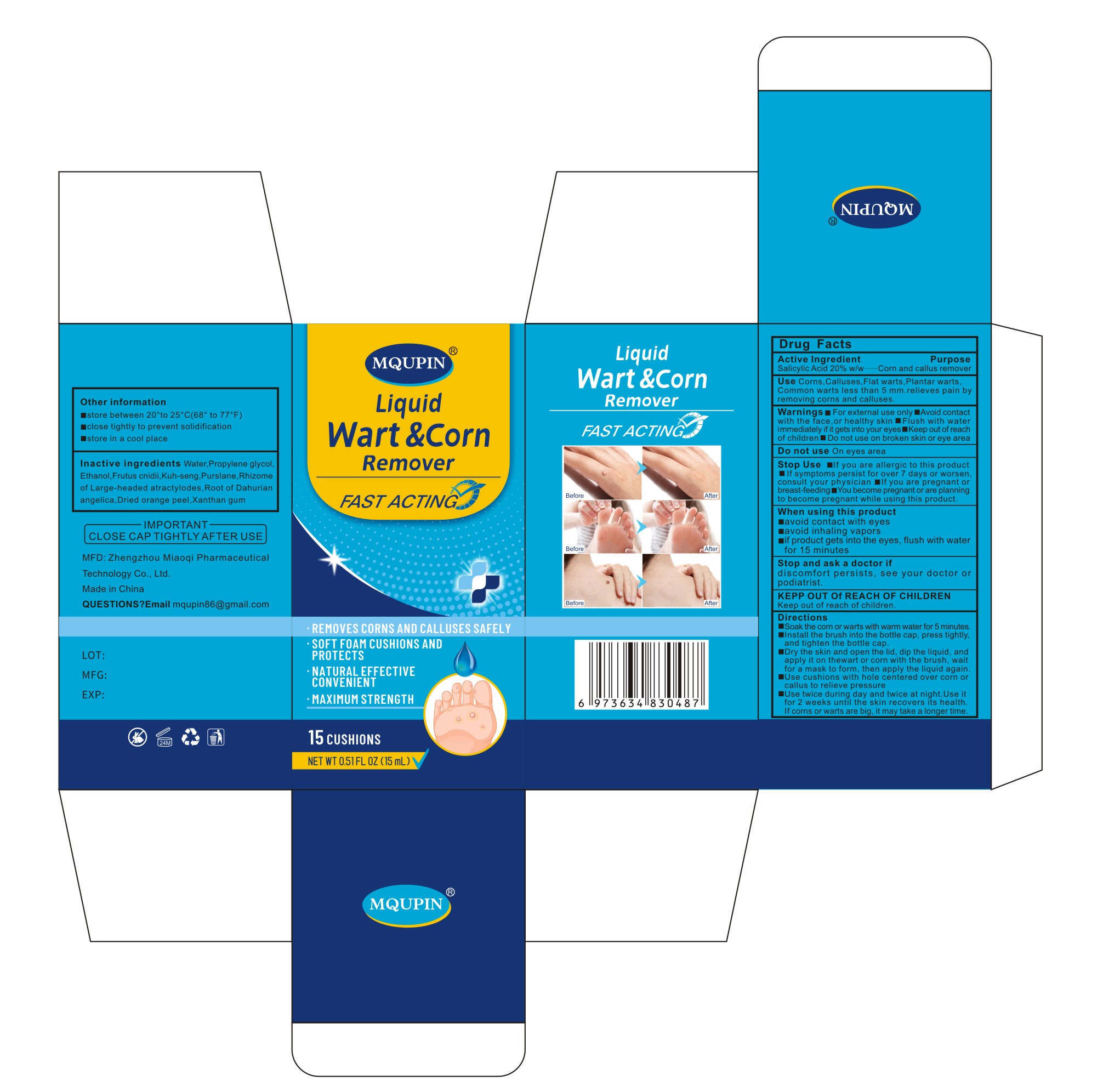 DRUG LABEL: Mqupin Liquid Wart Corn Remover
NDC: 83781-005 | Form: LIQUID
Manufacturer: Zhengzhou Miaoqi Pharmaceutical Technology Co., Ltd
Category: otc | Type: HUMAN OTC DRUG LABEL
Date: 20260128

ACTIVE INGREDIENTS: SALICYLIC ACID 20 g/100 mL
INACTIVE INGREDIENTS: PROPYLENE GLYCOL; ORANGE PEEL; WATER; CNIDIUM MONNIERI WHOLE; XANTHAN GUM; ALCOHOL; ATRACTYLODES LANCEA ROOT; PURSLANE; ANGELICA DAHURICA ROOT; SOPHORA FLAVESCENS ROOT

83781-005 Add 20ml 30ml

Active Ingredient

Salicylic Acid 20% w/w

Purpose

Corn and callus remover

Use

Use Corns, Calluses, Flat warts, Plantar warts, Common warts less than 5 mm.relieves pain by removing corns and calluses.

Warnings

■ For external use only

■ Avoid contact with the face, or healthy skin

■ Flush with water immediately if it gets into your eyes

■ Keep out of reach of children

■ Do not use on broken skin or eye area

Do not use

On eyes area

When Using

■ avoid contact with eyes
■ avoid inhaling vapors
■ if product gets into the eyes, flush with water for 15 minutes

Stop Use

■ If you are allergic to this product

■ If symptoms persist for over 7 days or worsen, consult your physician

■ If you are pregnant or breast-feeding

■ You become pregnant or are planning to become pregnant while using this product.

Ask Doctor

discomfort persists, see your doctor or podiatrist.

Keep Out Of Reach Of Children

Directions

■ Soak the corn or warts with warm water for 5 minutes.
■ Install the brush into the bottle cap, press tightly, and tighten the bottle cap.
■ Dry the skin and open the lid, dip the liquid, and apply it on thewart or corn with the brush, wait for a mask to form, then apply the liquid again.
■ Use cushions with hole centered over corn or callus to relieve pressure
■ Use twice during day and twice at night.Use it for 2 weeks until the skin recovers its health. If corns or warts are big, it may take a longer time.

Other information

■ store between 20°to 25°C (68° to 77°F)
■ close tightly to prevent solidification
■ store in a cool place

Questions

mqupin86@gmail.com

Inactive ingredients

Water, Propylene glycol, Ethanol, Frutus cnidii,Kuh-seng, Purslane, Rhizome of Large-headed atractylodes, Root of Dahurian angelica, Dried orange peel, Xanthan gum